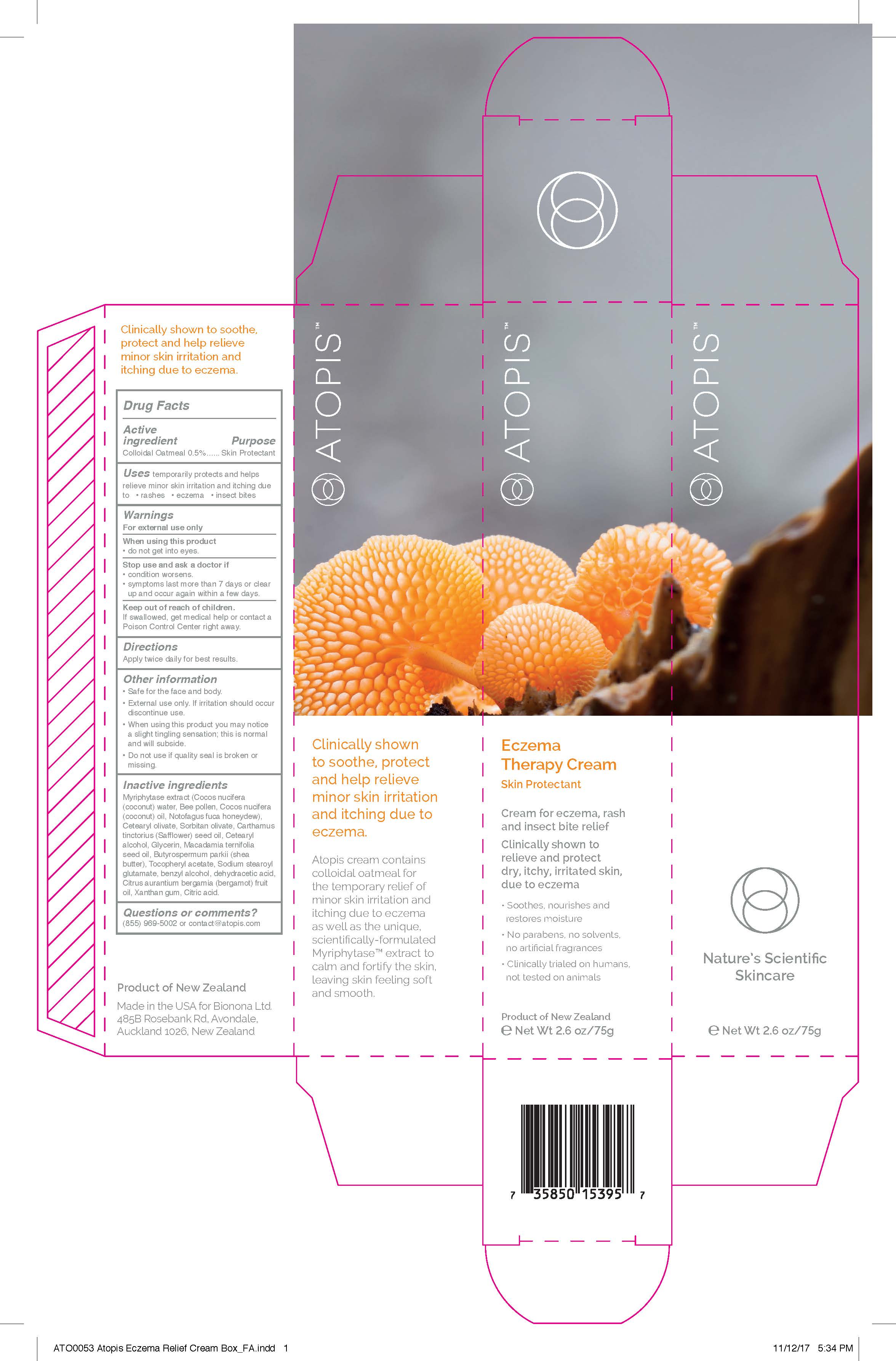 DRUG LABEL: Atopis Eczema Therapy Cream
NDC: 71570-001 | Form: CREAM
Manufacturer: Bionona Limited
Category: otc | Type: HUMAN OTC DRUG LABEL
Date: 20241212

ACTIVE INGREDIENTS: OATMEAL 0.5 g/100 g
INACTIVE INGREDIENTS: COCONUT WATER; BEE POLLEN; HONEYDEW MELON; SAFFLOWER OIL; DEHYDROACETIC ACID; BERGAMOT OIL; XANTHAN GUM; COCONUT OIL; CETEARYL OLIVATE; SORBITAN OLIVATE; CETOSTEARYL ALCOHOL; GLYCERIN; MACADAMIA OIL; SHEA BUTTER; ALPHA-TOCOPHEROL ACETATE; BENZYL ALCOHOL; ANHYDROUS CITRIC ACID; SODIUM STEAROYL GLUTAMATE

ACTIVE INGREDIENT

Colloidal Oatmeal 0.5%

PURPOSE

Colloidal Oatmeal 0.5%...... Skin Protectant

INDICATIONS AND USAGE

temporarily protects and helps relieve minor skin irritation and itching due to • rashes • eczema • insect bites

WARNINGS

For external use only

When using this product
• do not get into eyes.

Stop use and ask a doctor if
• condition worsens.
• symptoms last more than 7 days or clear up and occur again within a few days.

Keep out of reach of children.If swallowed, get medical help or contact a Poison Control Center right away.

DOSAGE AND ADMINISTRATION

Apply twice daily for best results.

STORAGE AND HANDLING

• Safe for the face and body.
• External use only. If irritation should occur discontinue use.
• When using this product you may notice a slight tingling sensation; this is normal and will subside.
• Do not use if quality seal is broken or missing.

INACTIVE INGREDIENT

Myriphytase extract (Cocos nucifera (coconut) water, Bee pollen, Cocos nucifera coconut) oil, Notofagus fuca honeydew), Cetearyl olivate, Sorbitan olivate, Carthamus tinctorius (Safflower) seed oil, Cetearyl alcohol, Glycerin, Macadamia ternifolia seed oil, Butyrospermum parkii (shea butter), Tocopheryl acetate, Sodium stearoyl glutamate, benzyl alcohol, dehydracetic acid, Citrus aurantium bergamia (bergamot) fruit oil, Xanthan gum, Citric acid.

QUESTIONS

(855) 969-5002 or contact@atopis.com

PACKAGE LABEL

ATOPIS

Eczema
Therapy Cream

Skin Protectant

Cream for eczema, rash and insect bite relief

Clinically shown to relieve and protect dry, itchy, irritated skin, due to eczema

• Soothes, nourishes and restores moisture
• No parabens, no solvents, no artificial fragrances
• Clinically trialed on humans, not tested on animals

Product of New Zealand
E Net Wt 2.6 oz/75g